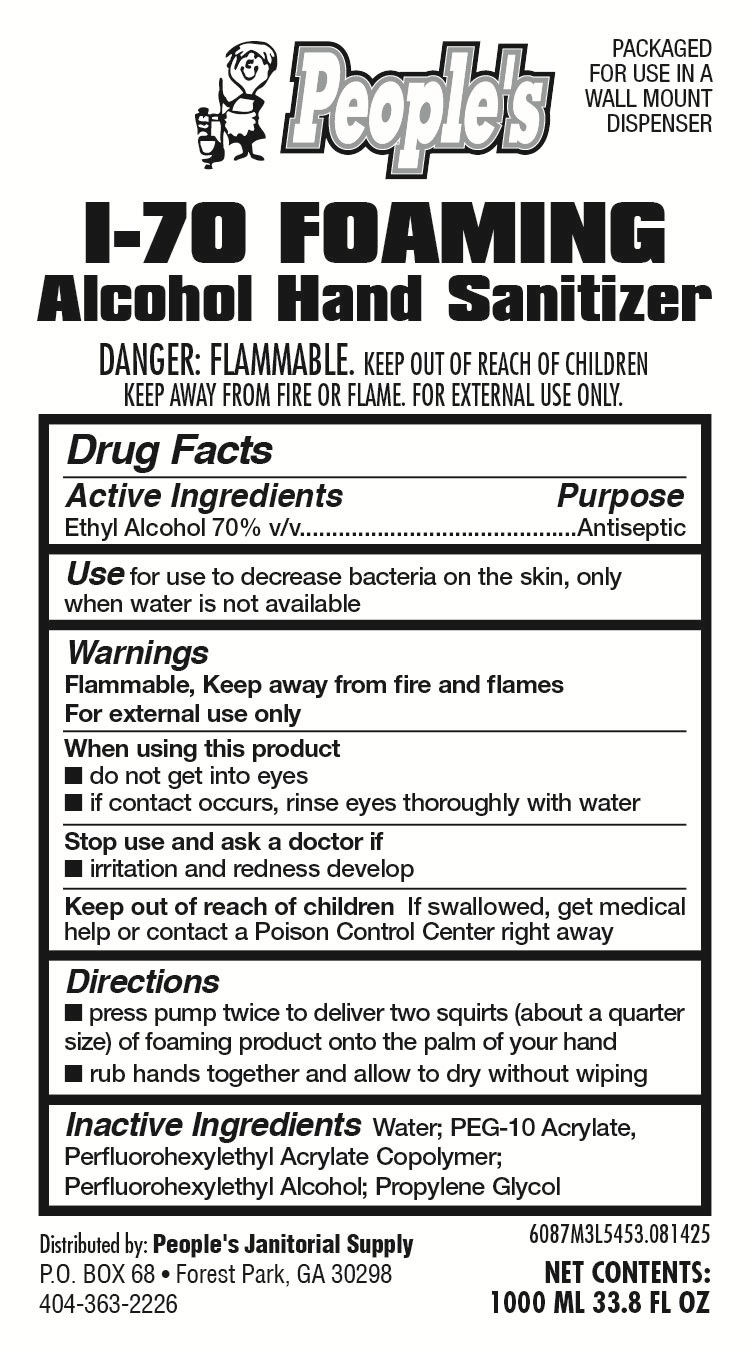 DRUG LABEL: I-70 Foaming
NDC: 43097-968 | Form: LIQUID
Manufacturer: People's Janitorial Supply
Category: otc | Type: HUMAN OTC DRUG LABEL
Date: 20250819

ACTIVE INGREDIENTS: ALCOHOL 0.7 mL/1 mL
INACTIVE INGREDIENTS: PEG-10 ACRYLATE/PERFLUOROHEXYLETHYL ACRYLATE COPOLYMER; 2-(PERFLUOROHEXYL)ETHANOL; WATER; PROPYLENE GLYCOL

I-70 Foam

ACTIVE INGREDIENT

Ethyl Alcohol 70%

PURPOSE

Antiseptic

WHEN USING

do not get into eyes
if contact occurs, rinse eyes thoroughly with water

Keep out of reach of children If swallowed, get medical help or contact a Poison Control Center right away

STOP USE

irritation and redness develop

Warnings
Flammable, Keep away from fire and flames
For external use only

Directions
press pump twice to deliver two squirts (about a quarter
size) of foaming product onto the palm of your hand
rub hands together and allow to dry without wiping

INACTIVE INGREDIENT

Water, PEG 10 Acrylate, Fluorohexylethyl acrylate copolymer, Perflourohexylethyl alcohol, propylene glycol

INDICATIONS AND USAGE

Use for use to decrease bacteria on the skin, only when water is not available